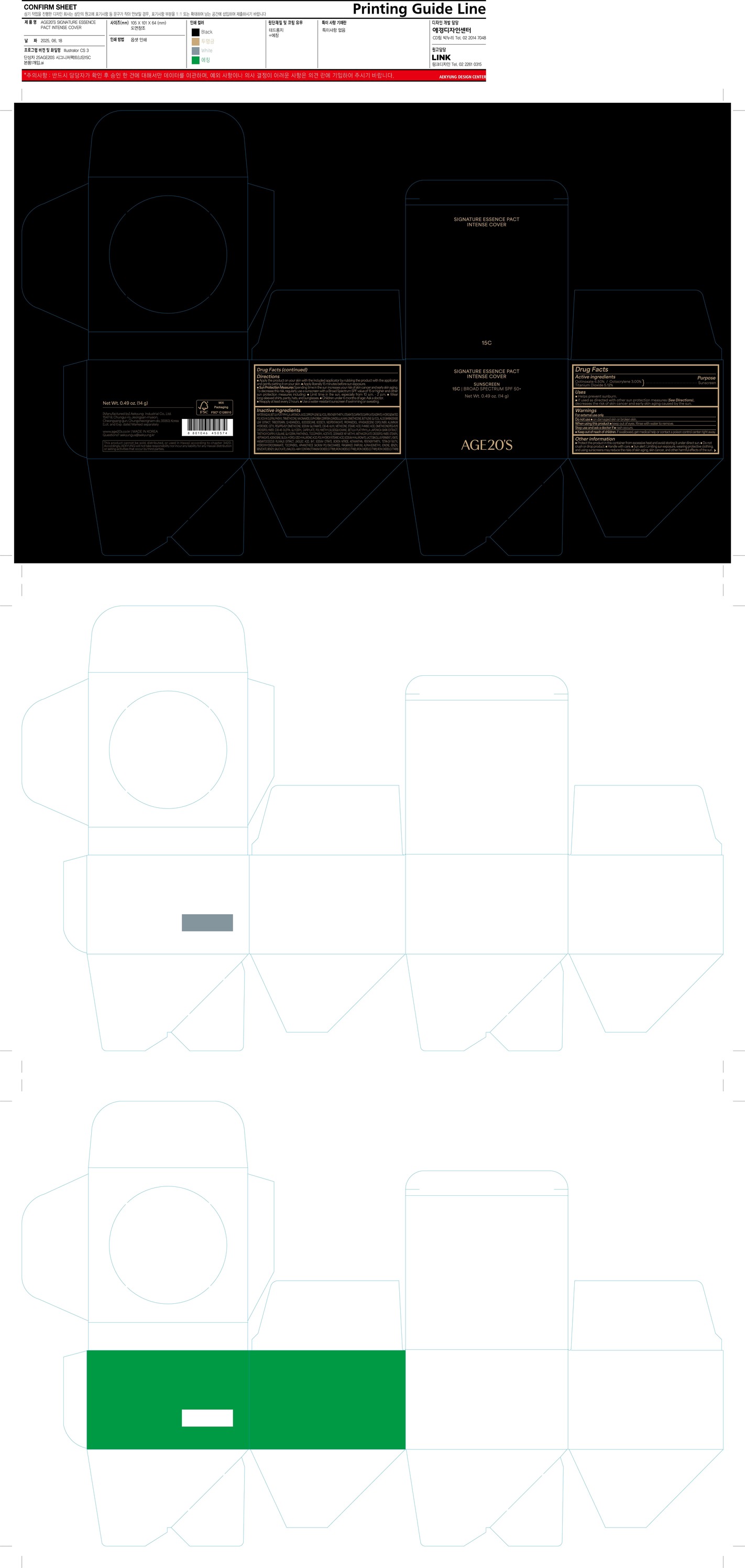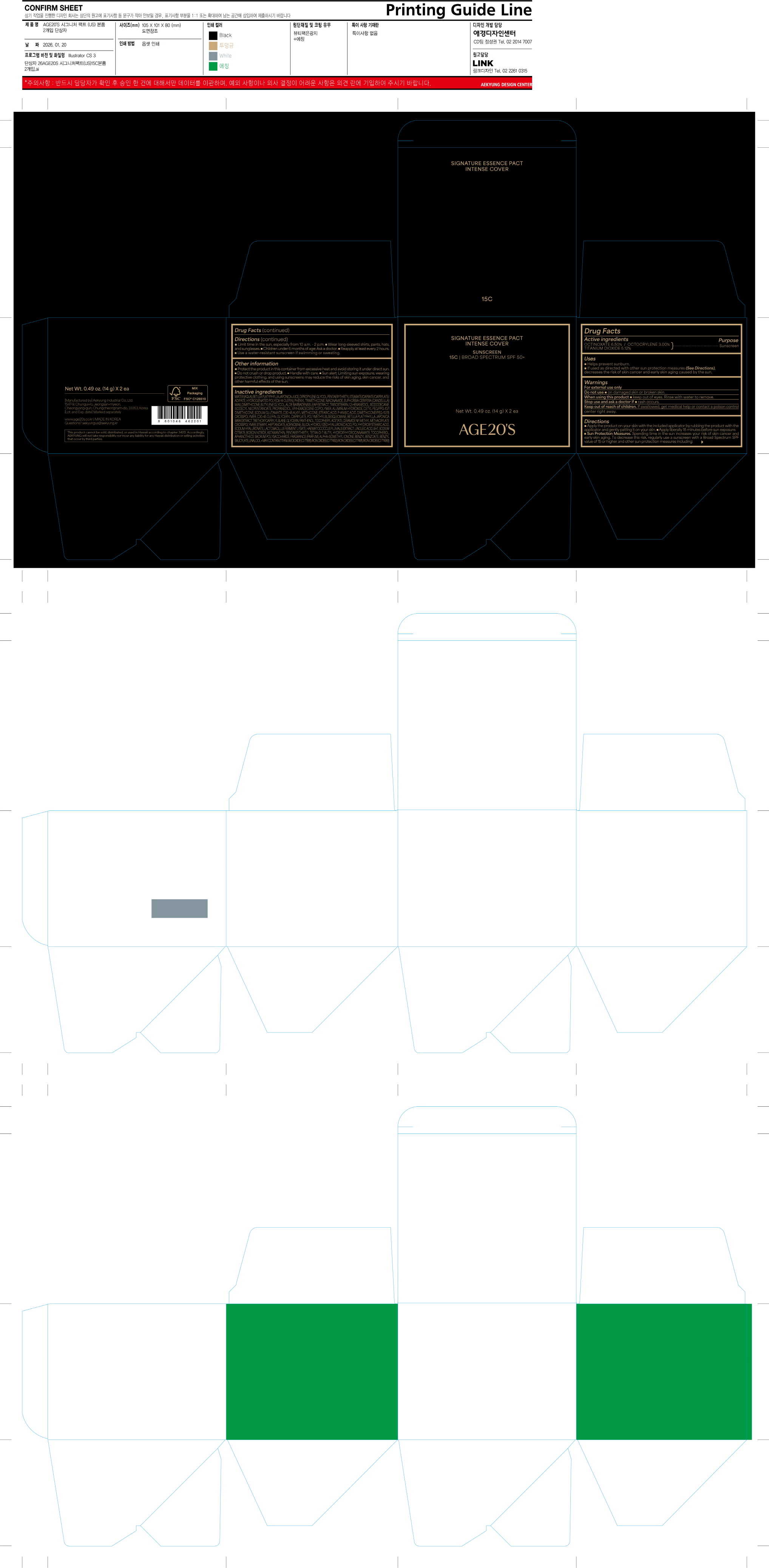 DRUG LABEL: AGE20S SIGNATURE ESSENCE PACT INTENSE COVER 15C
NDC: 67225-5203 | Form: CREAM
Manufacturer: Aekyung Industrial Co., Ltd.
Category: otc | Type: HUMAN OTC DRUG LABEL
Date: 20260121

ACTIVE INGREDIENTS: OCTOCRYLENE 0.42 g/14 g; TITANIUM DIOXIDE 0.7186 g/14 g; OCTINOXATE 0.91 g/14 g
INACTIVE INGREDIENTS: WATER; BETULA PLATYPHYLLA JAPONICA JUICE; DIPROPYLENE GLYCOL; HYDROGENATED POLY(C6-14 OLEFIN; 2 CST); PHENYL TRIMETHICONE; NIACINAMIDE; EUPHORBIA CERIFERA (CANDELILLA) WAX; DIMETHICONE; BUTYLENE GLYCOL; ALOE BARBADENSIS LEAF; TRIISOSTEARIN; 1,2-HEXANEDIOL; ISODODECANE; ISODECYL NEOPENTANOATE; PROPANEDIOL; VP/HEXADECENE COPOLYMER; ALUMINUM HYDROXIDE; CETYL PEG/PPG-10/1 DIMETHICONE (HLB 2); SODIUM GLUTAMATE; C30-45 ALKYL METHICONE; STEARIC ACID; P-ANISIC ACID; DIMETHICONE/PEG-10/15 CROSSPOLYMER; C30-45 OLEFIN; GLYCERYL CAPRYLATE; BETULA PLATYPHYLLA JAPONICA BARK; TRIETHOXYCAPRYLYLSILANE; POLYMETHYLSILSESQUIOXANE (11 MICRONS); GLYCERIN; PANTHENOL; .ALPHA.-TOCOPHEROL ACETATE, D-; CERAMIDE NP; METHYL METHACRYLATE/GLYCOL DIMETHACRYLATE CROSSPOLYMER; SILICA; STEARYL HEPTANOATE; ADENOSINE; HYALURONIC ACID; POLYHYDROXYSTEARIC ACID (2300 MW); SODIUM HYALURONATE; LIMOSILACTOBACILLUS FERMENTUM ME-3; HAEMATOCOCCUS PLUVIALIS; LINOLEIC ACID; BHT; SODIUM CITRATE; BORON NITRIDE; ASTAXANTHIN; PENTAERYTHRITYL TETRA-DI-T-BUTYL HYDROXYHYDROCINNAMATE; TOCOPHEROL; CI 77492; CI 77491; CI 77499

67225-5203 AGE20S SIGNATURE ESSENCE PACT INTENSE COVER 15C

ACTIVE INGREDIENT

Octinoxate 6.50%
Octocrylene 3.00%
Titanium Dioxide 5.12%

PURPOSE

Sunscreen

INDICATIONS AND USAGE

■ Helps prevent sunburn.

■ If used as directed with other sun protection measures (See Directions), decreases the risk of skin cancer and early skin aging caused by the sun.

WARNINGS

For external use only

DO NOT USE

■ damaged skin or broken skin

WHEN USING

■ keep out of eyes. Rinse with water to remove.

STOP USE

if ■ rash occurs.

KEEP OUT OF REACH OF CHILDREN

If swallowed, get medical help or contact poison control center right away.

Directions

■ Apply liberally 15 minutes before sun exposure.

■ Children under 6 months of age: Ask a doctor.

■ Reapply at least every 2 hours.

■ Use a water-resistant sunscreen if swimming or sweating

■ Sun Protection Measures. Spending time in the sun increases your risk of skin cancer and early skin aging. Todecrease this risk, regularly use a sunscreen with a Broad Spectrum SPF value of 15 or higher and other sun protection measures including:

■ Limit time in the sun, especially from 10 a.m. - 2 p.m.

■ Wear long-sleeved shirts, pants, hats, and sunglasses.

OTHER SAFETY INFORMATION

■ Protect the product in the container from excessive heat and avoid storing it under direct sun.

■ Sun alert: Limiting sun exposure, wearing protective clothing, and using sunscreens may reduce the risks of skin aging, skin cancer, and other harmful effects of the sun.

INACTIVE INGREDIENT

WATER (AQUA), ETHYLHEXYL METHOXYCINNAMATE, TITANIUM DIOXIDE (NANO), BETULA PLATYPHYLLA JAPONICA JUICE, DIPROPYLENE GLYCOL
PENTAERYTHRITYL STEARATE/CAPRATE/CAPRYLATE/ADIPATE, HYDROGENATED POLY(C6-14 OLEFIN), OCTOCRYLENE, PHENYL TRIMETHICONE
NIACINAMIDE, EUPHORBIA CERIFERA (CANDELILLA) WAX, DIMETHICONE, BUTYLENE GLYCOL, ALOE BARBADENSIS LEAF EXTRACT, TRIISOSTEARIN, 1,2-HEXANEDIOL, DISODODECANE, POLYMETHYLSILSESQUIOXANE, ISODECYL NEOPENTANOATE, PROPANEDIOL, VP/HEXADECENE COPOLYMER, ALUMINUM HYDROXIDE, CETYL PEG/PPG-10/1 DIMETHICONE, SODIUM GLUTAMATE, C30-45 ALKYL METHICONE, STEARIC ACID, P-ANISIC ACID, DIMETHICONE/PEG-10/15 CROSSPOLYMER, C30-45 OLEFIN, GLYCERYL CAPRYLATE, BETULA PLATYPHYLLA JAPONICA BARK EXTRACT, GLYCERIN, TRIETHOXYCAPRYLYLSILANE, PANTHENOL, TOCOPHERYL ACETATE, CERAMIDE NP, METHYL METHACRYLATE CROSSPOLYMER, STEARYL HEPTANOATE, ADENOSINE, SILICA, HYDROLYZED HYALURONIC ACID, POLYHYDROXYSTEARIC ACID, SODIUM HYALURONATE, LACTOBACILLUS FERMENT LYSATE, HAEMATOCOCCUS PLUVIALIS EXTRACT, LINOLEIC ACID, BHT, SODIUM CITRATE, BORON NITRIDE, ASTAXANTHIN, PENTAERYTHRITYL TETRA-DI-T-BUTYL, YDROXYHYDROCINNAMATE, TOCOPHEROL, APHANOTHECE SACRUM POLYSACCHARIDE, FRAGRANCE (PARFUM), Titanium Dioxide(CI 77891), IRON OXIDES (CI 77492), IRON OXIDES (CI 77491), IRON OXIDES (CI 77499)